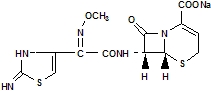 DRUG LABEL: Unknown
Manufacturer: Fujisawa Healthcare, Inc.
Category: prescription | Type: Human prescription drug label
Date: 20070804

Cefizox®
(CEFTIZOXIME FOR INJECTION, USP)

Fujisawa

To reduce the development of drug-resistant bacteria and maintain the effectiveness of Cefizox and other antibacterial drugs, Cefizox should be used only to treat or prevent infections that are proven or strongly suspected to be caused by bacteria.

FOR INTRAMUSCULAR

OR INTRAVENOUS USE

Description

Cefizox® (ceftizoxime for injection, USP) is a sterile, semisynthetic, broadspectrum, betalactamase resistant cephalosporin antibiotic for parenteral (IV, IM) administration. It is the sodium salt of [6R[6a,7β(Z)]]7[[(2,3dihydro2imino4 thiazolyl) (methoxyimino) acetyl] amino]8oxo5thia1azabicyclo [4.2.0] oct2ene2carboxylic acid. Its sodium content is approximately 60 mg (2.6 mEq) per gram of ceftizoxime activity.

It has the following structural formula:

C12H12N5NaO5S2 405.38

Ceftizoxime for injection, USP is a white to pale yellow crystalline powder.

Cefizox is supplied in vials equivalent to 500 mg, 1 gram or 2 grams of ceftizoxime, and in Piggyback Vials for IV admixture equivalent to 1 gram or 2 grams of ceftizoxime.

Clinical Pharmacology

The table below demonstrates the serum levels and duration of Cefizox (ceftizoxime for injection, USP) following IM administration of 500 mg and 1 gram doses, respectively, to normal volunteers.

Serum Concentrations After Intramuscular Administration Serum Concentration (μg/mL)
Dose | ½ hr | 1 hr | 2 hr | 4 hr | 6 hr | 8hr
500 mg | 13.3 | 13.7 | 9.2 | 4.8 | 1.9 | 0.7
1 gm | 36.0 | 39.0 | 31.0 | 15.0 | 6.0 | 3.0

Following IV administration of 1, 2, and 3 gram doses of Cefizox to normal volunteers, the following serum levels were obtained.

Serum Concentrations After Intravenous Administration Serum Concentration (μg/mL)
Dose | 5 min | 10 min | 30 min | 1 hr | 2 hr | 4 hr | 8 hr
1 gram | ND [ND=Not Done] | ND | 60.5 | 38.9 | 21.5 | 8.4 | 1.4
2 grams | 131.8 | 110.9 | 77.5 | 53.6 | 33.1 | 12.1 | 2.0
3 grams | 221.1 | 174.0 | 112.7 | 83.9 | 47.4 | 26.2 | 4.8

A serum halflife of approximately 1.7 hours was observed after IV or IM administration.

Cefizox is 30% protein bound.

Cefizox is not metabolized, and is excreted virtually unchanged by the kidneys in 24 hours. This provides a high urinary concentration. Concentrations greater than 6000 μg/mL have been achieved in the urine by 2 hours after a 1 gram dose of Cefizox intravenously. Probenecid slows tubular secretion and produces even higher serum levels, increasing the duration of measurable serum concentrations.

Cefizox achieves therapeutic levels in various body fluids, e.g., cerebrospinal fluid (in patients with inflamed meninges), bile, surgical wound fluid, pleural fluid, aqueous humor, ascitic fluid, peritoneal fluid, prostatic fluid and saliva, and in the following body tissues: heart, gallbladder, bone, biliary, peritoneal, prostatic, and uterine.

In clinical experience to date, no disulfiramlike reactions have been reported with Cefizox.

Microbiology

The bactericidal action of ceftizoxime results from inhibition of cellwall synthesis. Ceftizoxime is highly resistant to a broad spectrum of betalactamases (penicillinase and cephalosporinase), including Richmond types I, II, III, TEM, and IV, produced by both aerobic and anaerobic grampositive and gramnegative organisms. Ceftizoxime has been shown to be active against most strains of the following microorganisms, both in vitro and in clinical infections described in the INDICATIONS AND USAGE section:

Aerobic Gram-Positive Microorganisms

Staphylococcus aureus (including penicillinase producing strains)

NOTE: Methicillinresistant staphylococci are resistant to cephalosporins, including ceftizoxime.

Staphylococcus epidermidis (including penicillinase producing strains)

Streptococcus agalactiae

Streptococcus pneumoniae

Streptococcus pyogenes

NOTE: A streptococcal isolate that is susceptible to penicillin can be considered susceptible to ceftizoxime^4.

NOTE: Ceftizoxime is usually inactive against most strains of Enterococcus faecalis.

Aerobic Gram-Negative Microorganisms

Enterobacter spp.

Escherichia coli

Haemophilus influenzae (including ampicillinresistant strains)

Klebsiella pneumoniae

Morganella morganii

Neisseria gonorrhoeae

Proteus mirabilis

Proteus vulgaris

Providencia rettgeri

Pseudomonas aeruginosa

Serratia marcescens

Anaerobic Microorganisms

Bacteroides spp.

Peptococcus spp.

Peptostreptococcus spp.

The following in vitro data are available, but their clinical significance is unknown. At least 90% of the following microorganisms exhibit an in vitro minimum inhibitory concentration (MIC) less than or equal to the susceptible breakpoint for ceftizoxime. However, the safety and effectiveness of ceftizoxime in treating clinical infections due to these microorganisms have not been established in adequate and well-controlled clinical trials.

Aerobic Gram-Negative Microorganisms

Aeromonas hydrophila

Citrobacter spp.

Moraxellacatarrhalis

Neisseria meningitidis

Providencia stuartii

Susceptibility Testing Methods:

Dilution techniques:

Quantitative methods are used to determine antimicrobial minimum inhibitory concentrations (MICs). These MICs provide estimates of the susceptibility of bacteria to antimicrobial compounds. The MICs should be determined using a standardized procedure. Standardized procedures are based on a dilution method^1 (broth or agar) or equivalent with standardized inoculum concentrations and standardized concentrations of ceftizoxime powder. The MIC values should be interpreted according to the following criteria:

For testing non-fastidious aerobic microorganisms other than Haemophilus spp., Neisseria gonorrhoeae:
MIC (μg/mL) | Interpretation
≤8 | Susceptible (S)
16-32 | Intermediate (I)
≥64 | Resistant (R)

For testing Haemophilus spp. [These interpretative standards are applicable only to broth microdilution susceptibility testing with Haemophilus spp. using Haemophilus Test Medium.^2]
MIC (μg/mL) | Interpretation [The current absence of data on resistant strains precludes defining any category other than “susceptible”. Strains yielding MIC results suggestive of a “nonsusceptible” category should be submitted to a reference laboratory for further testing.]
≤2 | Susceptible (S)

For testing Neisseria gonorrhoeae [These interpretative standards are applicable only to agar dilution susceptibility testing using GC agar base and 1% defined growth supplements.]
MIC (μg/mL) | Interpretation [The current absence of data on resistant strains precludes defining any category other than “susceptible”. Strains yielding MIC results suggestive of a “nonsusceptible” category should be submitted to a reference laboratory for further testing.]
≤0.5 | Susceptible (S)

A report of “Susceptible” indicates that the pathogen is likely to be inhibited if the antimicrobial compound in the blood reaches the concentrations usually achievable. A report of “Intermediate” indicates that the result should be considered equivocal, and, if the microorganism is not fully susceptible to alternative, clinically feasible drugs, the test should be repeated. This category implies possible clinical applicability in body sites where the drug is physiologically concentrated or in situations where high dosage of drug can be used. This category also provides a buffer zone, which prevents small-uncontrolled technical factors from causing major discrepancies in interpretation. A report of “Resistant” indicates that the pathogen is not likely to be inhibited if the antimicrobial compound in the blood reaches the concentrations usually achievable, other therapy should be selected.

Standardized susceptibility test procedures require the use of laboratory control microorganisms to control the technical aspects of the laboratory procedures. Standard ceftizoxime powder should provide the following MIC values:

Microorganism | MIC(μg/mL)
Escherichia coli ATCC 25922 | 0.030.12
Haemophilus influenzae ATCC 49247 | 0.06-0.5
Neisseria gonorrhoeae ATCC 49226 | 0.008-0.03
Pseudomonas aeruginosa ATCC 27853 | 16-64
Staphylococcus aureus ATCC 29213 | 28

Diffusion Techniques:

Quantitative methods that require measurement of zone diameters also provide reproducible estimates of the susceptibility of bacteria to antimicrobial compounds. One such standardized procedure^2 requires the use of standardized inoculum concentrations. This procedure uses paper disks impregnated with 30-μg ceftizoxime to test the susceptibility of microorganisms to ceftizoxime.

Reports from the laboratory providing results of the standard single-disk susceptibility test with a 30-μg ceftizoxime disk should be interpreted according to the following criteria:

Zone diameter interpretative standard for testing non-fastidious aerobic microorganisms other than Haemophilus spp. and Neisseria gonorrhoeae:
Zone Diameter (mm) | Interpretation
≥ 20 | Susceptible (S)
15-19 | Intermediate (I)
≤ 14 | Resistant (R)

Zone diameter interpretative standard for Haemophilus spp. [These zone diameter standards are applicable only to susceptibility testing with Haemophilus spp. using Haemophilus Test Medium.^3]
Zone Diameter (mm) | Interpretation [The current absence of data on resistant strains precludes defining any category other than “susceptible”. Strains yielding MIC results suggestive of a “nonsusceptible” category should be submitted to a reference laboratory for further testing.]
≥ 26 | Susceptible (S)

Zone diameter interpretative standard for testing Neisseria gonorrhoeae. [These interpretative standards are applicable only to disk diffusion testing using GC agar base and 1% defined growth supplements incubated at 5% CO2.]
Zone Diameter (mm) | Interpretation [The current absence of data on resistant strains precludes defining any category other than “susceptible”. Strains yielding MIC results suggestive of a “nonsusceptible” category should be submitted to a reference laboratory for further testing.]
≥ 38 | Susceptible (S)

Interpretation should be as stated above for results using dilution techniques. Interpretation involves correlation of the diameter obtained in the disk test with the MIC for ceftizoxime.

As with standardized dilution techniques, diffusion methods require the use of laboratory control microorganisms that are used to control the technical aspects of the laboratory procedures. For the diffusion technique, the 30-μg ceftizoxime disk should provide the following zone diameters in these laboratory test quality control strains:

Microorganism | Zone Diameter (mm)
Escherichia coli ATCC 25922 | 30-36
Haemophilus influenzae ATCC 49247 | 29-39
Neisseria gonorrhoeae ATCC 49226 | 42-51
Pseudomonas aeruginosa ATCC 27853 | 12-17
Staphylococcus aureus ATCC 25923 | 27-35

Anaerobic Techniques:

For anaerobic bacteria, the susceptibility to ceftizoxime as MICs can be determined by standardized test methods. Agar dilution results can vary widely when using ceftizoxime. It is recommended that broth microdilution method be used when possible.^3 The MIC values obtained should be interpreted according to following criteria:

MIC(μg/mL)
Broth dilution | Agar dilution |  | Interpretation
≤ 16 | ≤ 32 |  | Susceptible (S)
32 | 64 |  | Intermediate (I)
≥ 64 | ≥ 128 |  | Resistant (R)

Interpretation is identical to that described in Susceptibility Testing: Dilution Techniques.

As with other susceptibility techniques, the use of laboratory control microorganisms is required to control the technical aspects of the laboratory standardized procedures. Standardized ceftizoxime powder should provide the following MIC values:

Microorganism | MIC(μg/mL)
 | Broth dilution | Agar dilution
Eubacterium lentum ATCC 43055 | 16-64 | 16-64
Bacteriodes thetaiotaomicron ATCC 29741 | --- | 4-16

Susceptibility Testing for Pseudomonas in Urinary Tract Infections

Most strains of Pseudomonas aeruginosa are moderately susceptible to ceftizoxime.

Ceftizoxime achieves high levels in the urine (greater than 6000 μg/mL at 2 hours with

1 gram IV) and, therefore, the following zone sizes should be used when testing

ceftizoxime for treatment of urinary tract infections caused by Pseudomonas

aeruginosa.

Susceptible organisms produce zones of 20 mm or greater, indicating that the

test organism is likely to respond to therapy.

Organisms that produce zones of 11 to 19 mm are expected to be susceptible

when the infection is confined to the urinary tract (in which high antibiotic levels

are attained).

Resistant organisms produce zones of 10 mm or less, indicating that other

therapy should be selected.

Indications and Usage

Cefizox (ceftizoxime for injection, USP) is indicated in the treatment of infections due to susceptible strains of the microorganisms listed below.

Lower Respiratory Tract Infections caused by Klebsiella spp.; Proteus mirabilis; Escherichia coli; Haemophilus influenzae including ampicillinresistant strains; Staphylococcus aureus (penicillinase and nonpenicillinaseproducing); Serratia spp.; Enterobacter spp.; Bacteroides spp.; and Streptococcus spp. including S. pneumoniae, but excluding enterococci.

Urinary Tract Infections caused by Staphylococcus aureus (penicillinase and nonpenicillinaseproducing); Escherichia coli; Pseudomonas spp. including P.aeruginosa; Proteus mirabilis; P. vulgaris; Providencia rettgeri (formerly Proteus rettgeri) and Morganella morganii (formerly Proteus morganii); Klebsiella spp.; Serratia spp. including S. marcescens; and Enterobacter spp.

Gonorrhea including uncomplicated cervical and urethral gonorrhea caused by Neisseria gonorrhoeae.

Pelvic Inflammatory Disease caused by Neisseria gonorrhoeae, Escherichia coli or Streptococcus agalactiae. NOTE: Ceftizoxime, like other cephalosporins, has no activity against Chlamydia trachomatis. Therefore, when cephalosporins are used in the treatment of patients with pelvic inflammatory disease and C. trachomatis is one of the suspected pathogens, appropriate antichlamydial coverage should be added.

IntraAbdominal Infections caused by Escherichia coli; Staphylococcusepidermidis; Streptococcus spp. (excluding enterococci); Enterobacter spp.; Klebsiella spp.; Bacteroides spp. including B. fragilis; and anaerobic cocci, including Peptococcus spp. and Peptostreptococcus spp.

Septicemia caused by Streptococcus spp. including S. pneumoniae (but excluding enterococci); Staphylococcus aureus (penicillinase and nonpenicillinaseproducing); Escherichia coli; Bacteroides spp. including B. fragilis; Klebsiella spp.; and Serratia spp.

Skin and Skin Structure Infections caused by Staphylococcus aureus (penicillinase and nonpenicillinaseproducing); Staphylococcus epidermidis; Escherichia coli; Klebsiella spp.; Streptococcus spp. including Streptococcus pyogenes (but excluding enterococci); Proteus mirabilis; Serratia spp.; Enterobacter spp.; Bacteroides spp. including B. fragilis; and anaerobic cocci, including Peptococcus spp. and Peptostreptococcus spp.

Bone and Joint Infections caused by Staphylococcus aureus (penicillinase and nonpenicillinaseproducing); Streptococcus spp. (excluding enterococci); Proteusmirabilis; Bacteroides spp.; and anaerobic cocci, including Peptococcus spp. and Peptostreptococcus spp.

Meningitis caused by Haemophilus influenzae. Cefizox has also been used successfully in the treatment of a limited number of pediatric and adult cases of meningitis caused by Streptococcus pneumoniae.

Cefizox has been effective in the treatment of seriously ill, compromised patients, including those who were debilitated, immunosuppressed, or neutropenic.

Infections caused by aerobic gramnegative and by mixtures of organisms resistant to other cephalosporins, aminoglycosides, or penicillins have responded to treatment with Cefizox.

Because of the serious nature of some urinary tract infections due to P. aeruginosa and because many strains of Pseudomonas species are only moderately susceptible to Cefizox, higher dosage is recommended. Other therapy should be instituted if the response is not prompt.

Susceptibility studies on specimens obtained prior to therapy should be used to determine the response of causative organisms to Cefizox. Therapy with Cefizox may be initiated pending results of the studies; however, treatment should be adjusted according to study findings. In serious infections, Cefizox has been used

concomitantly with aminoglycosides (see PRECAUTIONS). Before using Cefizox

concomitantly with other antibiotics, the prescribing information for those agents

should be reviewed for contraindications, warnings, precautions, and adverse reactions. Renal function should be carefully monitored.

To reduce the development of drug-resistant bacteria and maintain the effectiveness of Cefizox and other antibacterial drugs, Cefizox should be used only to treat or prevent infections that are proven or strongly suspected to be caused by susceptible bacteria. When culture and susceptibility information are available, they should be considered in selecting or modifying antibacterial therapy. In the absence of such data, local epidemiology and susceptibility patterns may contribute to the empiric selection of therapy.

CONTRAINDICATIONS

Cefizox (ceftizoxime for injection, USP) is contraindicated in patients who have known allergy to the drug.

WARNINGS

BEFORE THERAPY WITH CEFIZOX IS INSTITUTED, CAREFUL INQUIRY SHOULD BE MADE TO DETERMINE WHETHER THE PATIENT HAS HAD PREVIOUS HYPERSENSITIVITY REACTIONS TO CEFIZOX, OTHER CEPHALOSPORINS, PENICILLINS, OR OTHER DRUGS. IF THIS PRODUCT IS TO BE GIVEN TO PENICILLINSENSITIVE PATIENTS, CAUTION SHOULD BE EXERCISED BECAUSE CROSS HYPERSENSITIVITY AMONG BETALACTAM ANTIBIOTICS HAS BEEN CLEARLY DOCUMENTED AND MAY OCCUR IN UP TO 10% OF PATIENTS WITH A HISTORY OF PENICILLIN ALLERGY. IF AN ALLERGIC REACTION TO CEFIZOX OCCURS, DISCONTINUE THE DRUG. SERIOUS ACUTE HYPERSENSITIVITY REACTIONS MAY REQUIRE TREATMENT WITH EPINEPHRINE AND OTHER EMERGENCY MEASURES, INCLUDING OXYGEN, IV FLUIDS, IV ANTIHISTAMINES, CORTICOSTEROIDS, PRESSOR AMINES, AND AIRWAY MANAGEMENT, AS CLINICALLY INDICATED.

Pseudomembranous colitis has been reported with nearly all antibacterial agents, including ceftizoxime, and may range in severity from mild to life threatening. Therefore, it is important to consider this diagnosis in patients who present with diarrhea subsequent to the administration of antibacterial agents.

Treatment with antibacterial agents alters the normal flora of the colon and may permit overgrowth of clostridia. Studies indicate that a toxin produced by Clostridium difficile is a primary cause of “antibioticassociated” colitis.

After the diagnosis of pseudomembranous colitis has been established, appropriate therapeutic measures should be initiated. Mild cases of pseudomembranous colitis usually respond to drug discontinuation alone. In moderate to severe cases, consideration should be given to management with fluids and electrolytes, protein supplementation, and treatment with an antibacterial drug clinically effective against Clostridium difficile colitis.

Precautions

General

As with all broadspectrum antibiotics, Cefizox (ceftizoxime for injection, USP) should be prescribed with caution in individuals with a history of gastrointestinal disease, particularly colitis.

Although Cefizox has not been shown to produce an alteration in renal function, renal status should be evaluated, especially in seriously ill patients receiving maximum dose therapy. As with any antibiotic, prolonged use may result in overgrowth of nonsusceptible organisms. Careful observation is essential; appropriate measures should be taken if superinfection occurs.

Cephalosporins may be associated with a fall in prothrombin activity. Those at risk include patients with renal or hepatic impairment, or poor nutritional state, as well as patients receiving a protracted course of antimicrobial therapy, and patients previously stabilized on anticoagulant therapy. Prothrombin time should be monitored in patients at risk and exogenous vitamin K administered as indicated.

Prescribing Cefizox in the absence of a proven or strongly suspected bacterial infection or a prophylactic indication is unlikely to provide benefit to the patient and increases the risk of the development of drug-resistant bacteria.

Drug Interactions

Although the occurrence has not been reported with Cefizox, nephrotoxicity has been reported following concomitant administration of other cephalosporins and aminoglycosides.

Carcinogenesis, Mutagenesis, Impairment of Fertility

Longterm studies in animals to evaluate the carcinogenic potential of ceftizoxime have not been conducted.

In an in vitro bacterial cell assay (i.e., Ames test), there was no evidence of mutagenicity at ceftizoxime concentrations of 0.0010.5 mcg/plate. Ceftizoxime did not produce increases in micronuclei in the in vivo mouse micronucleus test when given to animals at doses up to 7500 mg/kg, approximately six times greater than the maximum human daily dose on a mg/M^2 basis.

Ceftizoxime had no effect on fertility when administered subcutaneously to rats at daily doses of up to 1000 mg/kg/day, approximately two times the maximum human daily dose on a mg/M^2 basis. Ceftizoxime produced no histological changes in the sexual organs of male and female dogs when given intravenously for thirteen weeks at a dose of 1000 mg/kg/day, approximately five times greater than the maximum human daily dose on a mg/M^2 basis.

Pregnancy

Teratogenic Effects: Pregnancy Category B.

Reproduction studies performed in rats and rabbits have revealed no evidence of impaired fertility or harm to the fetus due to Cefizox. There are, however, no adequate and wellcontrolled studies in pregnant women. Because animal reproduction studies are not always predictive of human effects, this drug should be used during pregnancy only if clearly needed.

Labor and Delivery

Safety of Cefizox use during labor and delivery has not been established.

Nursing Mothers

Cefizox is excreted in human milk in low concentrations. Caution should be exercised when Cefizox is administered to a nursing woman.

Pediatric Use

Safety and efficacy in pediatric patients from birth to six months of age have not been established. In pediatric patients six months of age and older, treatment with Cefizox has been associated with transient elevated levels of eosinophils, AST (SGOT), ALT (SGPT), and CPK (creatine phosphokinase). The CPK elevation may be related to IM administration.

The potential for the toxic effect in pediatric patients from chemicals that may leach from the singledose IV preparation in plastic has not been determined.

Geriatric Use

Clinical studies of ceftizoxime did not include sufficient numbers of subjects aged 65 and over to determine whether they respond differently from younger subjects. Other reported clinical experience has not identified differences in responses between the elderly and younger patients. In general, dose selection for an elderly patient should be cautious, usually starting at the low end of the dosing range, reflecting the greater frequency of decreased hepatic, renal, or cardiac function, and of concomitant disease or other drug therapy.

Information for Patients

Patients should be counseled that antibacterial drugs including Cefizox should only be used to treat bacterial infections. They do not treat viral infections (e.g., the common cold). When Cefizox is prescribed to treat a bacterial infection, patients should be told that although it is common to feel better early in the course of therapy, the medication should be taken exactly as directed. Skipping doses or not completing the full course of therapy may (1) decrease the effectiveness of the immediate treatment and (2) increase the likelihood that bacteria will develop resistance and will not be treatable by Cefizox or other antibacterial drugs in the future.

ADVERSE REACTIONS

Cefizox® (ceftizoxime for injection, USP) is generally well tolerated. The most frequent adverse reactions (greater than 1% but less than 5%) are:

Hypersensitivity--Rash, pruritus, fever.

Hepatic--Transient elevation in AST (SGOT), ALT (SGPT), and alkaline phosphatase.

Hematologic--Transient eosinophilia, thrombocytosis. Some individuals have developed a positive Coombs test.

Local--Injection site--Burning, cellulitis, phlebitis with IV administration, pain, induration, tenderness, paresthesia.

The less frequent adverse reactions (less than 1%) are:

Hypersensitivity--Numbness and anaphylaxis have been reported rarely.

Hepatic--Elevation of bilirubin has been reported rarely.

Renal--Transient elevations of BUN and creatinine have been occasionally observed with Cefizox.

Hematologic--Anemia, including hemolytic anemia with occasional fatal outcome, leukopenia, neutropenia, and thrombocytopenia have been reported rarely.

Urogenital--Vaginitis has occurred rarely.

Gastrointestinal--Diarrhea; nausea and vomiting have been reported occasionally.

Symptoms of pseudomembranous colitis can appear during or after antibiotic treatment (see WARNINGS).

In addition to the adverse reactions listed above which have been observed in patients treated with ceftizoxime, the following adverse reactions and altered laboratory tests have been reported for cephalosporinclass antibiotics:

StevensJohnson syndrome, erythema multiforme, toxic epidermal necrolysis, serumsickness like reaction, toxic nephropathy, aplastic anemia, hemorrhage, prolonged prothrombin time, elevated LDH, pancytopenia, and agranulocytosis.

Several cephalosporins have been implicated in triggering seizures, particularly in patients with renal impairment, when the dosage was not reduced. (See DOSAGE AND ADMINISTRATION.) If seizures associated with drug therapy occur, the drug should be discontinued. Anticonvulsant therapy can be given if clinically indicated.

DOSAGE AND ADMINISTRATION

The usual adult dosage is 1 or 2 grams of Cefizox (ceftizoxime for injection, USP) every 8 to 12 hours. Proper dosage and route of administration should be determined by the condition of the patient, severity of the infection, and susceptibility of the causative organisms.

General Guidelines for Dosage of Cefizox
Type of; Infection | Daily Dose; (Grams) | Frequency; and Route
Uncomplicated; Urinary Tract | 1 | 500 mg q12h IM or IV
Other Sites | 2-3 | 1 gram q8-12h IM or IV
Severe or; Refractory | 3-6 | 1 gram q8h IM or IV; 2 grams q8-12h IM [When administering 2 gram IM doses, the dose should be divided and given in different large muscle masses.] or IV
PID [If C. trachomatis is a suspected pathogen, appropriate antichlamydial coverage should be added, because ceftizoxime has no activity against this organism.] | 6 | 2 grams q8h IV
Life-Threatening [In lifethreatening infections, dosages up to 2 grams every 4 hours have been given.] | 9-12 | 3-4 grams q8h IV

______________________________________________________________________________

Because of the serious nature of urinary tract infections due to P. aeruginosa and because many strains of Pseudomonas species are only moderately susceptible to Cefizox, higher dosage is recommended. Other therapy should be instituted if the response is not prompt.

A single, 1 gram IM dose is the usual dose for treatment of uncomplicated gonorrhea.

The IV route may be preferable for patients with bacterial septicemia, localized parenchymal abscesses (such as intraabdominal abscess), peritonitis, or other severe or lifethreatening infections.

In those with normal renal function, the IV dosage for such infections is 2 to 12 grams of Cefizox (ceftizoxime for injection, USP) daily. In conditions such as bacterial septicemia, 6 to 12 grams/day may be given initially by the IV route for several days, and the dosage may then be gradually reduced according to clinical response and laboratory findings.

Pediatric Dosage Schedule
 | Unit Dose | Frequency
Pediatric patients; 6 months or older | 50 mg/kg | q6-8h

Dosage may be increased to a total daily dose of 200 mg/kg (not to exceed the maximum adult dose for serious infection).

Impaired Renal Function

Modification of Cefizox dosage is necessary in patients with impaired renal function. Following an initial loading dose of 500 mg-1 gram IM or IV, the maintenance dosing schedule shown below should be followed. Further dosing should be determined by therapeutic monitoring, severity of the infection, and susceptibility of the causative organisms.

When only the serum creatinine level is available, creatinine clearance may be calculated from the following formula. The serum creatinine level should represent current renal function at the steady state.

Males

Clcr =Weight (kg) x (140 age)

72 x serum creatinine

(mg/100 mL)

Females are 0.85 of the calculated clearance values for males.

In patients undergoing hemodialysis, no additional supplemental dosing is required following hemodialysis; however, dosing should be timed so that the patient receives the dose (according to the table below) at the end of the dialysis.

Dosage in Adults with Reduced Renal Function
Creatinine Clearance mL/min | Renal Function | Less Severe Infections | Life-Threatening Infections
79-50 | Mild; Impairment | 500 mg q8h | 0.75-1.5 grams; q8h
49-5 | Moderate; to severe; impairment | 250-500 mg; q12h | 0.5-1 gram; q12h
4-0 | Dialysis; Patients | 500 mg q48h; or; 250 mg q24h | 0.5-1 gram; q48h; or; 0.5 gram q24h

Preparation of Parenteral Solution

RECONSTITUTION

IM Administration: Reconstitute with Sterile Water for Injection. SHAKE WELL.

Vial Size | Diluent to Be Added | Approx. Avail. Vol. | Approx. Avg. Concentration | Room Temp. Stability
500 mg | 1.5 mL | 1.8 mL | 280 mg/mL | 16 hours
1 gram | 3.0 mL | 3.7 mL | 270 mg/mL | 16 hours
2 grams [When administering 2 gram IM doses, the dose should be divided and given in different large muscle masses.] | 6.0 mL | 7.4 mL | 270 mg/mL | 16 hours

IV Administration: Reconstitute with Sterile Water for Injection. SHAKE WELL.

Vial Size | Diluent to Be Added | Approx. Avail. Vol. | Approx. Avg. Concentration | Room Temp. Stability
500 mg | 5 mL | 5.3 mL | 95 mg/mL | 24 hours
1 gram | 10 mL | 10.7 mL | 95 mg/mL | 24 hours
2 grams | 20 mL | 21.4 mL | 95 mg/mL | 24 hours

These solutions of Cefizox are stable 24 hours at room temperature or 96 hours if refrigerated (5ºC).

Parenteral drug products should be inspected visually for particulate matter prior to administration. If particulate matter is evident in reconstituted fluids, then the drug solution should be discarded. Reconstituted solutions may range from yellow to amber without changes in potency.

Piggyback Vials: Reconstitute with 50 to 100 mL of Sodium Chloride Injection or any other IV solution listed below.

SHAKE WELL.

Administer with primary IV fluids, as a single dose. These Piggyback vial solutions of Cefizox are stable 24 hours at room temperature or 96 hours if refrigerated (5ºC).

A solution of 1 gram Cefizox in 13 mL Sterile Water for Injection is isotonic.

IM Injection

Inject well within the body of a relatively large muscle. Aspiration is necessary to avoid inadvertent injection into a blood vessel. When administering 2 gram IM doses, the dose should be divided and given in different large muscle masses.

IV Administration

Direct (bolus) injection, slowly over 3 to 5 minutes, directly or through tubing for patients receiving parenteral fluids (see list below). Intermittent or continuous infusion, dilute reconstituted Cefizox in 50 to 100 mL of one of the following solutions:

- Sodium Chloride Injection
- 5% or 10% Dextrose Injection
- 5% Dextrose and 0.9%, 0.45%, or 0.2% Sodium Chloride Injection
- Ringer’s Injection
- Lactated Ringer’s Injection
- Invert Sugar 10% in Sterile Water for Injection
- 5% Sodium Bicarbonate in Sterile Water for Injection
- 5% Dextrose in Lactated Ringer’s Injection (only when reconstituted with 4% Sodium Bicarbonate Injection)

In these fluids, Cefizox is stable 24 hours at room temperature or 96 hours if refrigerated (5ºC).

HOW SUPPLIED

Cefizox® (ceftizoxime for injection, USP)

NDC 0469725001 Product No. 725001

Equivalent to 500 mg ceftizoxime in 10 mL, singledose, fliptop vials, individually

packaged

NDC 0469725101 Product No. 725101

Equivalent to 1 gram ceftizoxime in 20 mL, singledose, fliptop vials, individually

packaged

NDC 0469725201 Product No. 725201

Equivalent to 1 gram ceftizoxime in 100 mL, singledose, Piggyback, fliptop vials, packaged in tens

NDC 0469725302 Product No. 725302

Equivalent to 2 grams ceftizoxime in 20 mL, singledose, fliptop vials, individually packaged

NDC 0469725402 Product No. 725402

Equivalent to 2 grams ceftizoxime in 100 mL, singledose, Piggyback, fliptop vials, packaged in tens

Unreconstituted Cefizox should be protected from excessive light, and stored at controlled room temperature (59º86ºF) in the original package until used.

Rx only

REFERENCES

1. National Committee for Clinical Laboratory Standards. Methods for Dilution Antimicrobial Susceptibility Tests for Bacteria that Grow Aerobically – Fifth Edition. Approved Standard NCCLS Document M7-A5, Vol. 20, No. 2, NCCLS, Wayne, PA, January 2000.
2. National Committee for Clinical Laboratory Standards. Performance Standards for Antimicrobial Disk Susceptibility Tests – Seventh Edition. Approved Standard NCCLS Document M2-A7, Vol. 20, No. 1, NCCLS, Wayne, PA, January 2000.
3. National Committee for Clinical Laboratory Standards. Methods for Antimicrobial Susceptibility Testing of Anaerobic Bacteria – Fourth Edition. Approved Standard NCCLS Document M11-A4, Vol. 17, No. 22, NCCLS, Wayne, PA, December 1997.
4. National Committee for Clinical Laboratory Standards. MIC Testing Supplemental Tables. NCCLS Document M100-S10 (M7), NCCLS, Wayne, PA, January 2000.

Product of Japan

Manufactured for:

Fujisawa Healthcare, Inc.

Deerfield, IL 60015-2548